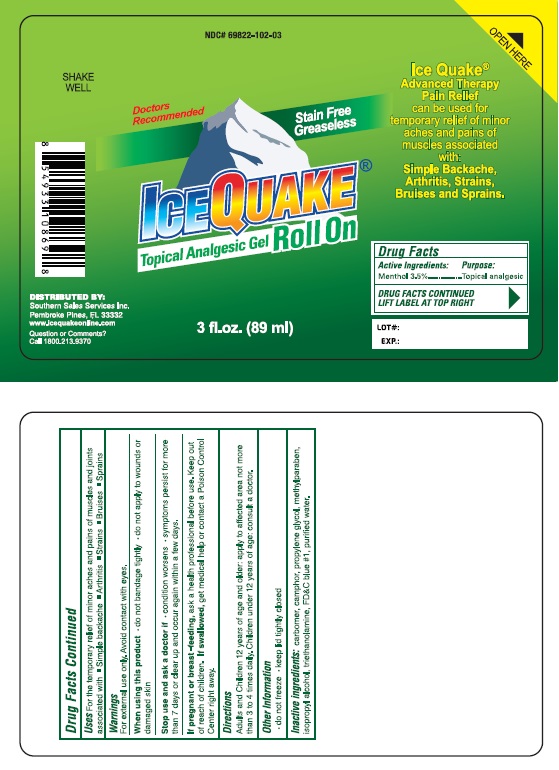 DRUG LABEL: Ice Quake Roll On
NDC: 69822-102 | Form: GEL
Manufacturer: Southern Sales & Service, Inc.
Category: otc | Type: HUMAN OTC DRUG LABEL
Date: 20170105

ACTIVE INGREDIENTS: MENTHOL 3.5 g/100 mL; CAMPHOR (NATURAL) 0.2 g/100 mL
INACTIVE INGREDIENTS: CARBOXYPOLYMETHYLENE; PROPYLENE GLYCOL; METHYLPARABEN; ISOPROPYL ALCOHOL; TROLAMINE; FD&C BLUE NO. 1; WATER

Gadaderm Frocen Ice FastmPain Releive

ACTIVE INGREDIENT

Active Ingredients | Purpose
Menthol 3.5% | Topical Analgesic
Camphor 0.2% | Topical Analgesic

INACTIVE INGREDIENT

Carbomer, Propylene Glycol, Methylparaben, Isopropyl Alcohol, Triethanolamine, FD&C Blue #1, Purified Water.

KEEP THIS AND ALL MEDICINE OUT OF REACH OF CHILDREN

In case of accidental ingestion, seek professional help and contact a Poison
Control Center inmediately.

WARNINGS

For the external use only. Use only as directed.

- Avoid contact with eyes.
- Do not use with other topical products.
- Do not use with heating device.
- Do not apply to open wounds or damaged skin.

Stop Use

- If condition worsens, or if symptoms persist for more than 7 days or clear up and occurs again within a few days, discontinue use of this product and consults a doctor.in.

Uses

For temporary relief of minor aches and pains of muscles and joints associated with simple backache, arthritis, strains, bruises, sprains.

DOSAGE & ADMINISTRATION

Adults and children 12 years and older.

- Apply to painful muscles and joints.
- Gently massage thoroughly into affected area.
- Repeat as necessary but no more than 4 times daily

PURPOSE

Topical Analgesic

Other Information:

Store at room temperaturewith cap closed tightly.

Distribute by:

SSS Group, LLC.

Pembroke Pines, FL 33332

www.icequakeonline.com

Questions or Comments?

1 800.213.9370